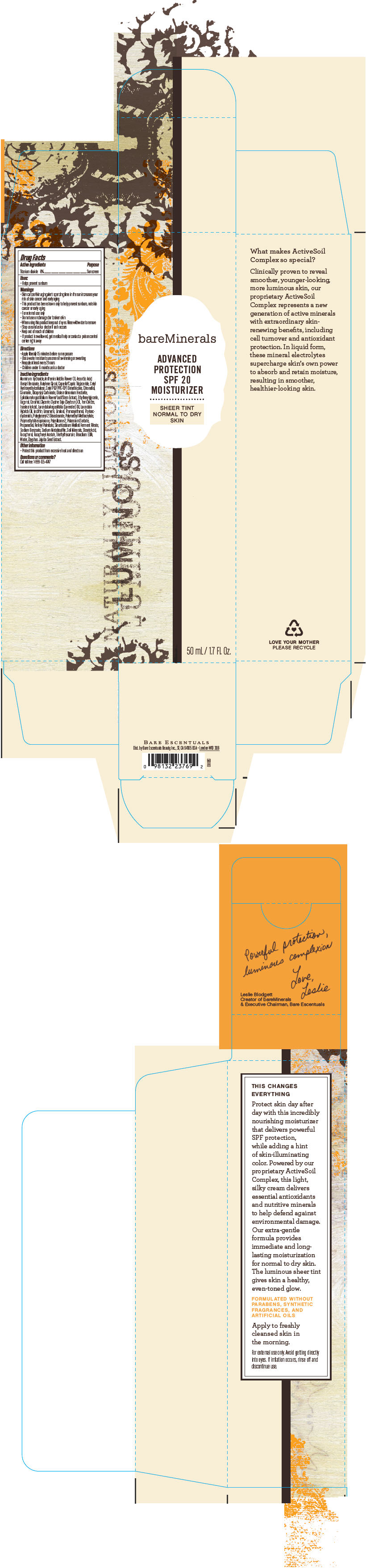 DRUG LABEL: bareMinerals Advanced Protection SPF 20 Moisturizer 
NDC: 98132-723 | Form: LOTION
Manufacturer: Bare Escentuals Beauty, Inc.
Category: otc | Type: HUMAN OTC DRUG LABEL
Date: 20140211

ACTIVE INGREDIENTS: Titanium Dioxide 60 mg/1 mL
INACTIVE INGREDIENTS: Aluminum Hydroxide; Chamaemelum Nobile Flower Oil; Ascorbic Acid; Benzyl Benzoate; Butylene Glycol; Medium-Chain Triglycerides; .Beta.-Citronellol, (R)-; Coumarin; Dicaprylyl Carbonate; Disteardimonium Hectorite; Epilobium Angustifolium Flowering Top; Ethylhexylglycerin; Eugenol; Geraniol; Glycerin; Soybean Oil; Ferric Oxide Red; Isostearic Acid; Lavender Oil; Lavandin Oil; Linalool, (+/-)-; Phenoxyethanol; Polyglyceryl-2 Diisostearate; Potassium Sorbate; Propanediol; Vitamin A Palmitate; Sodium Benzoate; Sodium Metabisulfite; Stearic Acid; Tocopherol; .Alpha.-Tocopherol Acetate; Triethylhexanoin; Edetate Trisodium; Water; Jujube Seed

bareMinerals Advanced Protection SPF 20 Moisturizer
Sheer Tint Normal to Dry Skin

Drug Facts

Active ingredients

Titanium dioxide 6%

Purpose

Sunscreen

Uses

- Helps prevent sunburn

Warnings

- Skin cancer/skin aging alert: spending time in the sun increases your risk of skin cancer and early aging
- This product has been shown only to help prevent sunburn, not skin cancer or early aging
- For external use only

- Do not use on damaged or broken skin

- When using this product keep out of eyes. Rinse with water to remove

- Stop use and ask a doctor if rash occurs

- Keep out of reach of children
- If product is swallowed, get medical help or contact a poison control center right away

Directions

- Apply liberally 15 minutes before sun exposure
- Use a water resistant sunscreen if swimming or sweating
- Reapply at least every 2 hours
- Children under 6 months: ask a doctor

Inactive ingredients

Aluminum Hydroxide, Anthemis Nobilis Flower Oil, Ascorbic Acid, Benzyl Benzoate, Butylene Glycol, Caprylic/Capric Triglyceride, Cetyl Hydroxyethylcellulose, Cetyl PEG/PPG-10/1 Dimethicone, Citronellol, Coumarin, Dicaprylyl Carbonate, Disteardimonium Hectorite, Epilobium Angustifolium Flower/Leaf/Stem Extract, Ethylhexylglycerin, Eugenol, Geraniol, Glycerin, Glycine Soja (Soybean) Oil, Iron Oxides, Isostearic Acid, Lavandula Angustifolia (Lavender) Oil, Lavandula Hybrida Oil, Lecithin, Limonene, Linalool, Phenoxyethanol, Phytoecdysteroids, Polyglyceryl-2 Diisostearate, Polymethyl Methacrylate, Polymethylsilsesquioxane, Polysilicone-2, Potassium Sorbate, Propanediol, Retinyl Palmitate, Sinorhizobium Meliloti Ferment Filtrate, Sodium Benzoate, Sodium Metabisulfite, Soil Minerals, Stearic Acid, Tocopherol, Tocopheryl Acetate, Triethylhexanoin, Trisodium EDTA, Water, Zizyphus Jujuba Seed Extract.

Other information

- Protect this product from excessive heat and direct sun

Questions or comments?

Call toll free 1-888-795-4747

Dist. by Bare Escentuals Beauty, Inc., SF, CA 94105 USA

PRINCIPAL DISPLAY PANEL - 50 mL Bottle Box

bareMinerals

ADVANCED
PROTECTION
SPF 20
MOISTURIZER

SHEER TINT
NORMAL TO DRY
SKIN

50 mL / 1.7 Fl. Oz.